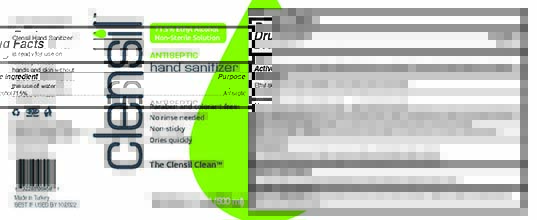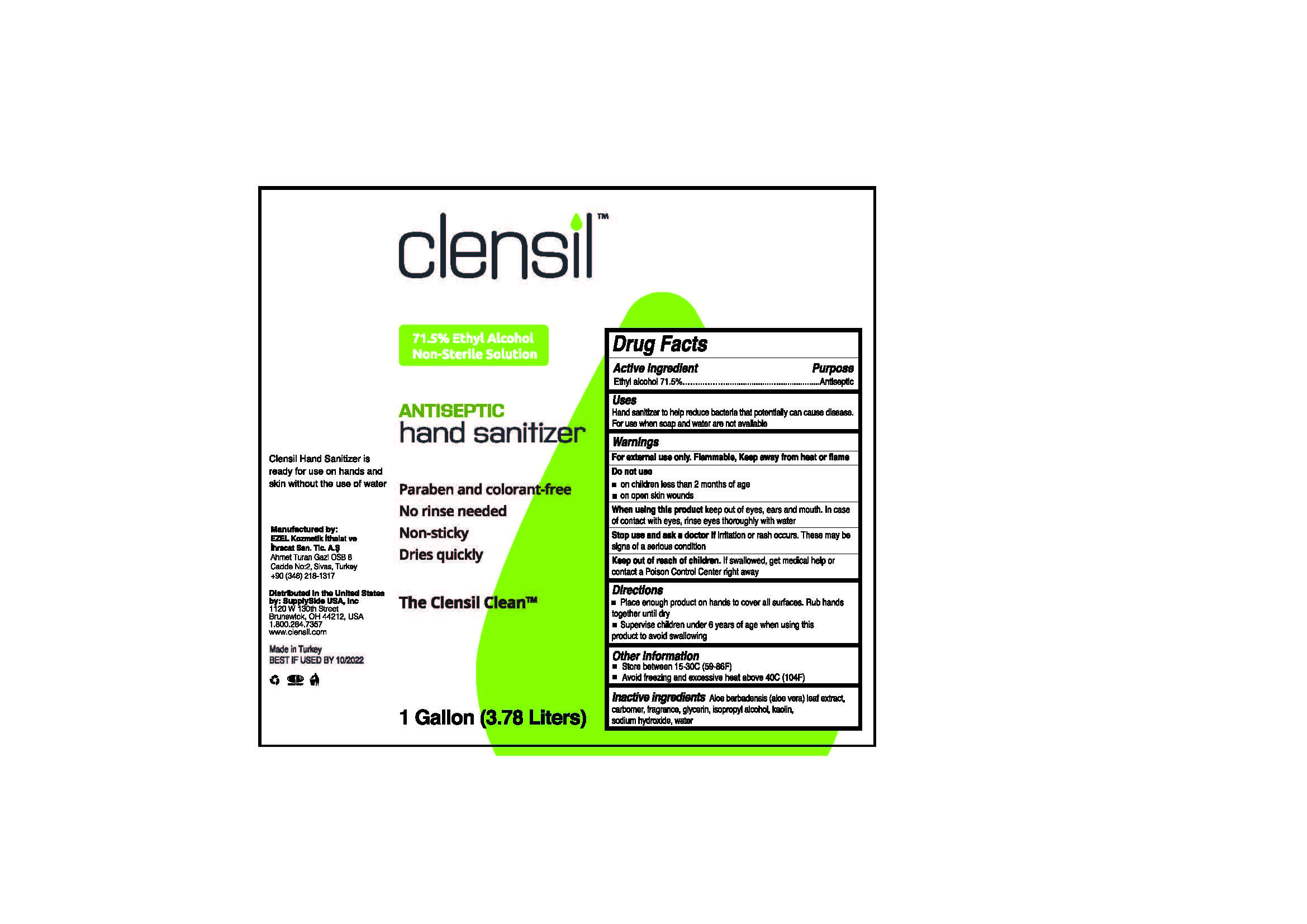 DRUG LABEL: Clensil
NDC: 75801-999 | Form: GEL
Manufacturer: EZEL KOZMETIK ITH. VE IHR. TIC. VE SAN. A.Ş.
Category: otc | Type: HUMAN OTC DRUG LABEL
Date: 20230617

ACTIVE INGREDIENTS: ALCOHOL 71.5 mL/100 mL
INACTIVE INGREDIENTS: ALOE VERA LEAF POLYSACCHARIDES; GLYCERIN; WATER; SODIUM HYDROXIDE 0.01 mL/100 mL; ISOPROPYL ALCOHOL 2 mL/100 mL; CARBOMER 940; KAOLIN

This is a hand sanitizer manufactured according to the OTC Monograph published in April 2019.

The hand sanitizer is manufactured using only the following United States Pharmacopoeia (USP) grade ingredients in the preparation of the product (percentage in final product formulation)

1. Alcohol (ethanol) (USP or Food Chemical Codex (FCC) grade) (71.5%, volume/volume (v/v)) in an aqueous solution denatured according to Alcohol and Tobacco Tax and Trade Bureau regulations in 27 CFR part 20.
2. Glycerine (inactive)
3. Water (inactive)
4. Isopropyl alcohol (2% volume/volume (v/v)) (inactive)
5. Sodium hydroxide (0.01% (v/v)) (inactive)

The firm does not add other active or inactive ingredients. Different or additional ingredients may impact the quality and potency of the product.

Active Ingredient(s)

Alcohol 71.5% v/v. Purpose: Antiseptic

Purpose

Antiseptic, Hand Sanitizer

Use

For hand sanitizing to decrease bacteria on the skin

Warnings

Flammable. Keep away from fire or flame

For external use only

Do not use on damaged, inflamed or broken skin

WHEN USING

Avoid contact with eyes. In case of eye contact, rinse eyes thoroughly with water
Stop use and ask a doctor if irritation or rash develops and lasts for more than 72 hrs
Keep out of reach of children. If swallowed, get medical help or contact a Poison Control Center right away

Stop use and ask a doctor if irritation or rash develops and lasts more than 72 hours

Keep out of reach of children. If swallowed, get medical help or contact a Poison Control Center right away.

Directions

- Wet hands thoroughly with product
- allow to dry without wiping

Other information

- keep out of direct sunlight
- Store in cool, dry conditions

Inactive ingredients

glycerin, water, isopropyl alcohol, sodium hydroxide

Use

Use for hand sanitizing to decrease bacteria on the skin

Package Label - Principal Display Panel

3785mL BOTTLE NDC: 75801-999-37